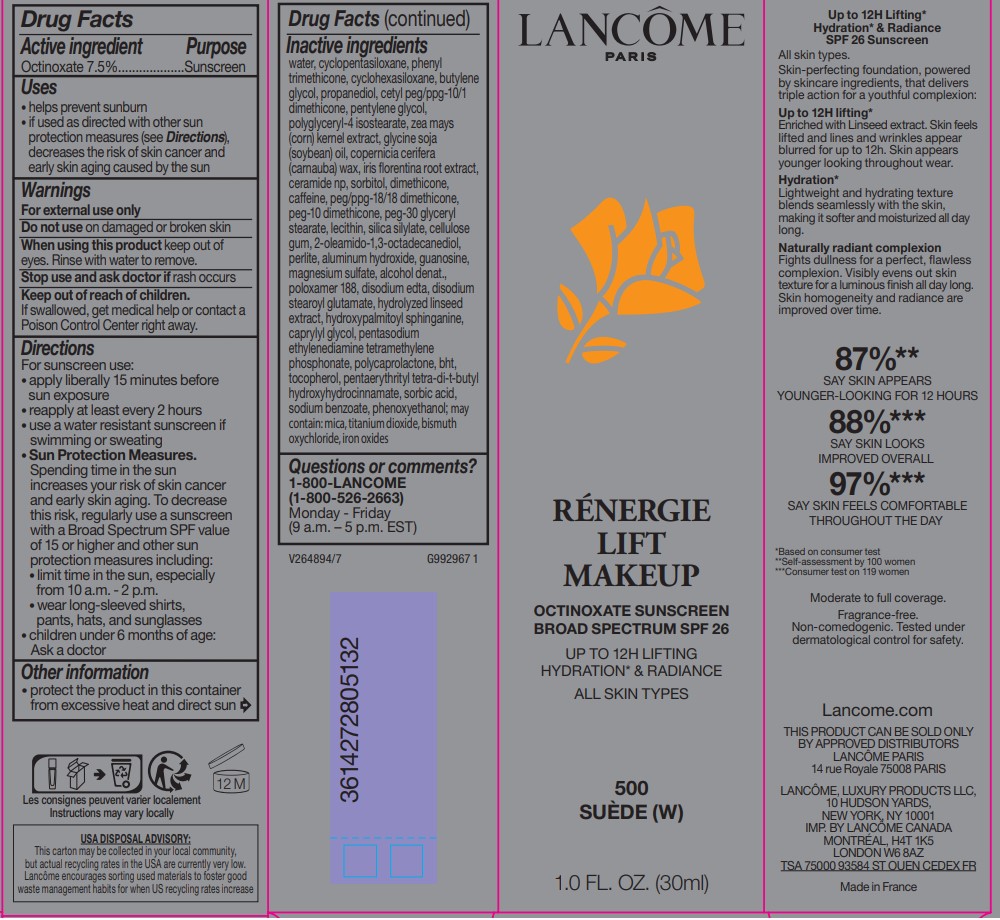 DRUG LABEL: Lancome Paris Renergie Lift Makeup Broad Spectrum SPF 26 Sunscreen
NDC: 49967-132 | Form: LIQUID
Manufacturer: L'Oreal USA Products Inc
Category: otc | Type: HUMAN OTC DRUG LABEL
Date: 20241223

ACTIVE INGREDIENTS: OCTINOXATE 75 mg/1 mL
INACTIVE INGREDIENTS: WATER; CYCLOMETHICONE 5; PHENYL TRIMETHICONE; CYCLOMETHICONE 6; BUTYLENE GLYCOL; PROPANEDIOL; CETYL PEG/PPG-10/1 DIMETHICONE (HLB 1.5); PENTYLENE GLYCOL; POLYGLYCERYL-4 ISOSTEARATE; CORN; SOYBEAN OIL; CARNAUBA WAX; IRIS X GERMANICA NOTHOVAR. FLORENTINA ROOT; CERAMIDE NP; SORBITOL; DIMETHICONE; CAFFEINE; PEG/PPG-18/18 DIMETHICONE; PEG-10 DIMETHICONE (600 CST); PEG-30 GLYCERYL STEARATE; ANILERIDINE; CELLULOSE GUM; 2-OLEAMIDO-1,3-OCTADECANEDIOL; PERLITE; ALUMINUM HYDROXIDE; GUANOSINE; MAGNESIUM SULFATE, UNSPECIFIED FORM; CINNAMIC ACID; ALCOHOL; POLOXAMER 188; EDETATE DISODIUM; DISODIUM STEAROYL GLUTAMATE; HYDROXYPALMITOYL SPHINGANINE; CAPRYLYL GLYCOL; LEXIDRONAM PENTASODIUM; BHT; TOCOPHEROL; PENTAERYTHRITOL TETRAKIS(3-(3,5-DI-TERT-BUTYL-4-HYDROXYPHENYL)PROPIONATE); SORBIC ACID; SODIUM BENZOATE; PHENOXYETHANOL; TITANIUM DIOXIDE; MICA; BISMUTH OXYCHLORIDE; FERRIC OXIDE RED

Drug Facts

Active ingredients

Octinoxate 7.5%

Purpose

Sunscreen

Uses

- helps prevent sunburn
- if used as directed with other sun protection measures (see Directions), decreases the risk of skin cancer and early skin aging caused by the sun

Warnings

For external use only

Do not use

on damaged or broken skin

When using this product

keep out of eyes. Rinse with water to remove.

Stop use and ask a doctor if

rash occurs

Keep out of reach of children.

If swallowed, getmedical help or contact a Poison Control Center right away.

Directions

For sunscreen use:

● apply liberally 15 minutes before sun exposure

● reapply at least every 2 hours

● use a water resistant sunscreen if swimming or sweating

● Sun Protection Measures. Spending time in the sun increases your risk of skin cancer and early skin aging. To decrease this risk, regularly use a sunscreen with a Broad Spectrum SPF value of 15 or higher and other sun protection measures including:

● limit time in the sun, especially from 10 a.m. – 2 p.m.

● wear long-sleeved shirts, pants, hats, and sunglasses

● children under 6 months of age: Ask a doctor

Other information

protect the product in this container from excessive heat and direct sun

Inactive ingredients

water, cyclopentasiloxane, phenyl trimethicone, cyclohexasiloxane, butylene glycol, propanediol, cetyl PEG/PPG-10/1 dimethicone, pentylene glycol, polyglyceryl-4 isostearate, zea mays (corn) kernel extract, glycine soja (soybean) oil, copernicia cerifera (carnauba) wax, iris florentina root extract, ceramide NP, sorbitol, dimethicone, caffeine, PEG/PPG-18/18 dimethicone,PEG-10 dimethicone, PEG-30 glyceryl stearate, lecithin, silica silylate, cellulose gum, 2-oleamido-1,3-octadecanediol, perlite, aluminum hydroxide, guanosine, magnesium sulfate, alcohol denat., poloxamer 188, disodium EDTA, disodium stearoyl glutamate, hydrolyzed linseed extract, hydroxypalmitoyl sphinganine,caprylyl glycol, pentasodium ethylenediamine tetramethylene phosphonate, polycaprolactone, BHT, tocopherol, pentaerytrityl tetra-di-t-butyl hydroxyhydrocinnamate, sorbic acid, sodium benzoate, phenoxyethanol; may contain: mica, titanium dioxide, bismuth oxychloride, iron oxides

Questions or comments?

1-800-LANCOME (1-800-526-2663) Monday - Friday (9 a.m. - 5 p.m. EST)